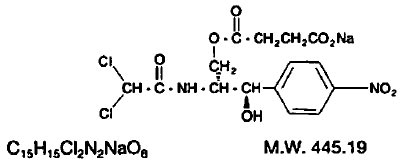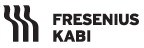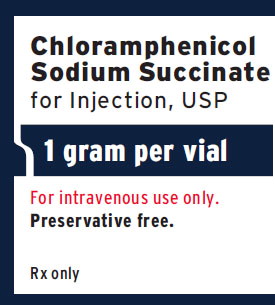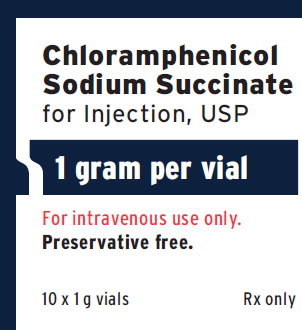 DRUG LABEL: Chloramphenicol Sodium Succinate

NDC: 63323-011 | Form: INJECTION, POWDER, LYOPHILIZED, FOR SOLUTION
Manufacturer: Fresenius Kabi USA, LLC
Category: prescription | Type: HUMAN PRESCRIPTION DRUG LABEL
Date: 20241010

ACTIVE INGREDIENTS: CHLORAMPHENICOL SODIUM SUCCINATE 1 g/10 mL

Chloramphenicol Sodium Succinate for Injection, USP

Rx only
FOR INTRAVENOUS ADMINISTRATION

WARNING

Serious and fatal blood dyscrasias (aplastic anemia, hypoplastic anemia, thrombocytopenia and granulocytopenia) are known to occur after the administration of chloramphenicol. In addition, there have been reports of aplastic anemia attributed to chloramphenicol which later terminated in leukemia. Blood dyscrasias have occurred after both short-term and prolonged therapy with this drug. Chloramphenicol must not be used when less potentially dangerous agents will be effective, as described in the INDICATIONS AND USAGEsection. It must not be used in the treatment of trivial infections or where it is not indicated, as in colds, influenza, infections of the throat; or as a prophylactic agent to prevent bacterial infections.

Precautions: It is essential that adequate blood studies be made during treatment with the drug. While blood studies may detect early peripheral blood changes, such as leukopenia, reticulocytopenia, or granulocytopenia, before they become irreversible, such studies cannot be relied on to detect bone marrow depression prior to development of aplastic anemia. To facilitate appropriate studies and observation during therapy, it is desirable that patients be hospitalized.

IMPORTANT CONSIDERATIONS IN PRESCRIBING INJECTABLE CHLORAMPHENICOL SODIUM SUCCINATE. CHLORAMPHENICOL SODIUM SUCCINATE IS INTENDED FOR INTRAVENOUS USE ONLY. IT HAS BEEN DEMONSTRATED TO BE INEFFECTIVE WHEN GIVEN INTRAMUSCULARLY.

- Chloramphenicol sodium succinate must be hydrolyzed to its microbiologically active form, and there is a lag in achieving adequate blood levels compared with the base given intravenously.
- Patients started on intravenous chloramphenicol sodium succinate should be changed to the oral form of another appropriate antibiotic as soon as practicable.

DESCRIPTION:

Chloramphenicol is an antibiotic that is clinically useful for, and should be reserved for, serious infections caused by organisms susceptible to its antimicrobial effects when less potentially hazardous therapeutic agents are ineffective or contraindicated. Sensitivity testing is essential to determine its indicated use, but may be performed concurrently with therapy initiated on clinical impression that one of the indicated conditions exists (see INDICATIONS AND USAGE section).

When reconstituted as directed, each vial contains a sterile solution equivalent to 100 mg of chloramphenicol per mL (1 g/10 mL).

Each gram (10 mL of a 10% solution) of chloramphenicol sodium succinate contains approximately 52 mg (2.25 mEq) of sodium.

The chemical name for chloramphenicol sodium succinate is D-threo-(-)-2, 2-Dichloro-N-[β-hydroxy-α-(hydroxymethyl)-p-nitrophenethyl] acetamide α-(sodium succinate).

The structural formula is:

CLINICAL PHARMACOLOGY:

Chloramphenicol administered orally is absorbed rapidly from the intestinal tract. In controlled studies in adult volunteers using the recommended dosage of 50 mg/kg/day, a dosage of 1 g every 6 hours for 8 doses was given. Using the microbiological assay method, the average peak serum level was 11.2 mcg/mL one hour after the first dose. A cumulative effect gave a peak rise to 18.4 mcg/mL after the fifth dose of 1 g. Mean serum levels ranged from 8 to 14 mcg/mL over the 48-hour period. Total urinary excretion of chloramphenicol in these studies ranged from a low of 68% to a high of 99% over a three-day period. From 8% to 12% of the antibiotic excreted is in the form of free chloramphenicol; the remainder consists of microbiologically inactive metabolites, principally the conjugate with glucuronic acid. Since the glucuronide is excreted rapidly, most chloramphenicol detected in the blood is in the microbiologically active free form. Despite the small proportion of unchanged drug excreted in the urine, the concentration of free chloramphenicol is relatively high, amounting to several hundred mcg/mL in patients receiving divided doses of 50 mg/kg/day. Small amounts of active drug are found in bile and feces. Chloramphenicol diffuses rapidly, but its distribution is not uniform. Highest concentrations are found in liver and kidney, and lowest concentrations are found in brain and cerebrospinal fluid. Chloramphenicol enters cerebrospinal fluid even in the absence of meningeal inflammation, appearing in concentrations about half of those found in the blood. Measurable levels are also detected in pleural and in ascitic fluids, saliva, milk, and in the aqueous and vitreous humors. Transport across the placental barrier occurs with somewhat lower concentration in cord blood of neonates than in maternal blood.

Microbiology

Mechanism of Action

Chloramphenicol is a broad-spectrum antibiotic originally isolated from Streptomyces venezuelae. It inhibits bacterial protein synthesis by interfering with the transfer of activated amino acids from soluble RNA to ribosomes. In vitro, chloramphenicol exerts mainly a bacteriostatic effect on a wide range of gram-negative and gram-positive bacteria.

Antimicrobial Activity

Chloramphenicol has been shown to be active against most strains of the following microorganisms, both in vitro and in clinical infections as described in the INDICATIONS AND USAGE section.

Aerobic gram-negative microorganisms

Haemophilus influenzae

Salmonella species, including Salmonella typhi

Other microorganisms

Lymphogranuloma-psittacosis group

Rickettsia

Susceptibility Testing Methods

When available, the clinical microbiology laboratory should provide cumulative reports of in vitro susceptibility test results for antimicrobial drugs used in local hospitals and practice areas to the physician as periodic reports that describe the susceptibility profile of nosocomial and community-acquired pathogens. These reports should aid the physician in selecting an antibacterial drug for treatment.

Dilution Techniques

Quantitative methods are used to determine antimicrobial minimum inhibitory concentrations (MICs). These MICs provide estimates of the susceptibility of bacteria to antimicrobial compounds. The MICs should be determined using a standardized (broth and/or agar).^1,3 The MIC values should be interpreted according to the criteria provided in Table 1.

Diffusion Techniques

Quantitative methods that require measurement of zone diameters can also provide reproducible estimates of the susceptibility of bacteria to antimicrobial compounds. The zone size should be determined using a standardized test method.^2,3 This procedure uses paper disks impregnated with 30 mcg chloramphenicol to test the susceptibility of bacteria to chloramphenicol. The disc diffusion breakpoints should be interpreted according to the criteria provided in Table 1.

Table 1. Susceptibility Test Interpretive Criteria for Chloramphenicol
Pathogen | Minimum Inhibitory Concentrations (mcg/mL) |  |  | Zone Diameters (mm)
Pathogen | S | I | R | S | I | R
Salmonella spp. | < 8 | 16 | > 32 | > 18 | 13 to 17 | < 12
Haemophilus influenzae | < 2 | 4 | > 8 | ≥ 29 | 26 to 28 | < 25

A report of Susceptible (S) indicates that the antimicrobial drug is likely to inhibit growth of the pathogen if the antimicrobial drug reaches the concentration usually achievable at the site of infection. A report of Intermediate (I) indicates that the result should be considered equivocal, and, if the microorganism is not fully susceptible to alternative, clinically feasible drugs, the test should be repeated. This category implies possible clinical applicability in body sites where the drug is physiologically concentrated or in situations where a high dosage of the drug can be used. This category also provides a buffer zone that prevents small uncontrolled technical factors from causing major discrepancies in interpretation. A report of Resistant (R) indicates that the antimicrobial drug is not likely to inhibit growth of the pathogen if the antimicrobial drug reaches the concentration usually achievable at the infection site; other therapy should be selected.

Quality Control

Standardized susceptibility test procedures require the use of laboratory controls to monitor and ensure the accuracy and precision of supplies and reagents used in the assay, and the techniques of the individuals performing the test.^1,2,3 Standard chloramphenicol powder should provide the following range of MIC values noted in Table 2. For the disc diffusion technique using the 30 mcg disk, the criteria in Table 2 should be achieved.

Table 2. Quality Control Parameters for Chloramphenicol
QC Strain |  | Minimum Inhibitory Concentrations (mcg/mL) |  | Zone Diameters (mm)
Escherichia coli ATCC 25922 |  | 2 to 8 |  | 21 to 27
Haemophilus influenzae ATCC 49247 |  | 0.25 to 1 |  | 31 to 40

INDICATIONS AND USAGE:

In accord with the concepts in the Warning Boxand this INDICATIONS AND USAGEsection, chloramphenicol must be used only in those serious infections for which less potentially dangerous drugs are ineffective or contraindicated. However, chloramphenicol may be chosen to initiate antibiotic therapy on the clinical impression that one of the conditions below is believed to be present; in vitro sensitivity tests should be performed concurrently so that the drug may be discontinued as soon as possible if less potentially dangerous agents are indicated by such tests. The decision to continue use of chloramphenicol rather than another antibiotic when both are suggested by in vitro studies to be effective against a specific pathogen should be based upon severity of the infection, susceptibility of the pathogen to the various antimicrobial drugs, efficacy of the various drugs in the infection, and the important additional concepts contained in the Warning Boxabove.

•Acute infections caused by Salmonella typhi*

It is not recommended for the routine treatment of the typhoid carrier state.

•Serious infections caused by susceptible strains in accordance with the concepts expressed above:

a) Salmonella species

b) H. influenzae, specially meningeal infections

c) Rickettsia

d) Lymphogranuloma-psittacosis group

e) Various gram-negative bacteria causing bacteremia, meningitis or other serious gram-negative infections.

f) Other susceptible organisms which have been demonstrated to be resistant to all other appropriate antimicrobial agents.

•Cystic fibrosis regimens

*In treatment of typhoid fever some authorities recommend that chloramphenicol be administered at therapeutic levels for 8 to 10 days after the patient has become afebrile to lessen the possibility of relapse.

CONTRAINDICATIONS:

Chloramphenicol is contraindicated in individuals with a history of previous hypersensitivity and/or toxic reaction to it. It must not be used in the treatment of trivial infections or where it is not indicated, as in colds, influenza, infections of the throat; or as a prophylactic agent to prevent bacterial infections.

PRECAUTIONS:

General

Repeated courses of chloramphenicol treatment should be avoided if at all possible. Treatment should not be continued longer than required to produce a cure with little or no risk or relapse of the disease.

Excessive blood levels may result from administration of the recommended dose to patients with impaired liver or kidney function. The dosage should be adjusted accordingly, or preferably, the blood concentration should be determined at appropriate intervals.

The use of this antibiotic, as with other antibiotics, may result in an overgrowth of nonsusceptible organisms, including fungi. If infections caused by nonsusceptible organisms appear during therapy, appropriate measures should be taken.

Laboratory Tests

Baseline blood studies should be followed by periodic blood studies approximately every two days during therapy. The drug should be discontinued upon appearance of reticulocytopenia, leukopenia, thrombocytopenia, anemia or any other blood study findings attributable to chloramphenicol. However, it should be noted that such studies do not exclude the possible later appearance of the irreversible type of bone marrow depression.

Drug Interactions

Concurrent therapy with other drugs that may cause bone marrow depression should be avoided.

Carcinogenesis, Mutagenesis, Impairment of Fertility

No studies have been conducted in animals or humans to evaluate the possibility of these effects with chloramphenicol.

Pregnancy

Pregnancy Category C –

Animal reproduction studies have not been conducted with chloramphenicol. There are no adequate and well-controlled studies to establish safety of this drug in pregnancy. It is not known whether chloramphenicol can cause fetal harm when administered to a pregnant woman. Orally administered chloramphenicol has been shown to cross the placental barrier. Because of potential toxic effects on the fetus (see ADVERSE REACTIONS,“Gray Syndrome”), chloramphenicol should be given to a pregnant woman only if the potential benefit justifies the potential risk to the fetus.

Nursing Mothers

Chloramphenicol is excreted in human milk following oral administration of the drug. Because of the potential for serious adverse reactions in nursing infants from chloramphenicol, a decision should be made whether to discontinue nursing or to discontinue the drug, taking into account the importance of the drug to the mother (see ADVERSE REACTIONS,“Gray Syndrome”).

Pediatric Use

Precaution should be used in therapy of premature and full-term neonates and infants to avoid “gray syndrome” toxicity. Due to immature metabolic processes in the neonate and infant, excessive blood levels may result from administration of the recommended dose. The dosage should be adjusted accordingly or, preferable, the blood concentration should be determined at appropriate intervals (see ADVERSE REACTIONS, "Gray Syndrome").

See DOSAGE AND ADMINISTRATION for dosing information in the pediatric population.

Geriatric Use

Clinical studies of chloramphenicol sodium succinate did not include sufficient numbers of subjects aged 65 and over to determine whether they respond differently from younger subjects. Other reported clinical experience has not identified differences in responses between the elderly and younger patients. In general, dose selection for an elderly patient should be cautious, usually starting at the low end of the dosing range, reflecting the greater frequency of decreased hepatic, renal, or cardiac function, and of concomitant disease or other drug therapy. This drug is known to be substantially excreted by the kidney, and the risk of toxic reactions to this drug may be greater in patients with impaired renal function. Because elderly patients are more likely to have decreased renal function, care should be taken in dose selection, and it may be useful to monitor renal function.

Each gram (10 mL of a 10% solution) of chloramphenicol sodium succinate contains approximately 52 mg (2.25 mEq) of sodium.

ADVERSE REACTIONS:

Blood Dyscrasias

The most serious adverse effect of chloramphenicol is bone marrow depression. Serious and fatal blood dyscrasias (aplastic anemia, hypoplastic anemia, thrombocytopenia, and granulocytopenia) are known to occur after the administration of chloramphenicol. An irreversible type of marrow depression leading to aplastic anemia with a high rate of mortality is characterized by the appearance weeks or months after therapy of bone marrow aplasia or hypoplasia. Peripherally, pancytopenia is most often observed, but in a small number of cases only one or two of the three major cell types (erythrocytes, leukocytes, platelets) may be depressed.

A reversible type of bone marrow depression, which is dose related, may occur. This type of marrow depression is characterized by vacuolization of the erythroid cells, reduction of reticulocytes and leukopenia, and responds promptly to the withdrawal of chloramphenicol.

An exact determination of the risk of serious and fatal blood dyscrasias is not possible because of lack of accurate information regarding 1) the size of the population at risk, 2) the total number of drug-associated dyscrasias, and 3) the total number of non-drug associated dyscrasias.

In a report to the California State Assembly by the California Medical Association and the State Department of Public Health in January 1967, the risk of fatal aplastic anemia was estimated at 1:24,200 to 1:40,500 based on two dosage levels.

There have been reports of aplastic anemia attributed to chloramphenicol which later terminated in leukemia.

Paroxysmal nocturnal hemoglobinuria has been reported.

Gastrointestinal Reactions

Nausea, vomiting, glossitis and stomatitis, diarrhea and enterocolitis may occur in low incidence.

Neurotoxic Reactions

Headache, mild depression, mental confusion, and delirium have been described in patients receiving chloramphenicol. Optic and peripheral neuritis have been reported, usually following long-term therapy. If this occurs, the drug should be promptly withdrawn.

Hypersensitivity Reactions

Fever, macular and vesicular rashes, angioedema, urticaria, and anaphylaxis may occur. Herxheimer’s reactions have occurred during therapy for typhoid fever.

"Gray Syndrome"

Toxic reactions including fatalities have occurred in the premature and neonate; the signs and symptoms associated with these reactions have been referred to as the “gray syndrome.” One case of gray syndrome has been reported in a neonate born to a mother having received chloramphenicol during labor. One case has been reported in a 3-month-old infant. The following summarizes the clinical and laboratory studies that have been made on these patients:

a) In most cases therapy with chloramphenicol had been instituted within the first 48 hours of life.

b) Symptoms first appeared after 3 to 4 days of continued treatment with high doses of chloramphenicol.

c) The symptoms appeared in the following order:

(1) abdominal distension with or without emesis;

(2) progressive pallid cyanosis;

(3) vasomotor collapse, frequently accompanied by irregular respiration;

(4) death within a few hours of onset of these symptoms.

d) The progression of symptoms from onset to exitus was accelerated with higher dose schedules.

e) Preliminary blood serum level studies revealed unusually high concentrations of chloramphenicol (over 90 mcg/mL after repeated doses).

f) Termination of therapy upon early evidence of the associated symptomatology frequently reversed the process with complete recovery.

DOSAGE AND ADMINISTRATION:

Chloramphenicol, like other potent drugs, should be prescribed at recommended doses known to have therapeutic activity. Administration of 50 mg/kg/day in divided doses will produce blood levels of the magnitude to which the majority of susceptible microorganisms will respond.

As soon as feasible an oral dosage form of another appropriate antibiotic should be substituted for intravenous chloramphenicol sodium succinate.

The following method of administration is recommended:

Intravenously as a 10% (100 mg/mL) solution to be injected over at least a one-minute interval. This is prepared by the addition of 10 mL of an aqueous diluent such as water for injection or 5% dextrose injection.

Adults

Adults should receive 50 mg/kg/day in divided doses at 6-hour intervals. In exceptional cases patients with infections due to moderately resistant organisms may require increased dosage up to 100 mg/kg/day to achieve blood levels inhibiting the pathogen, but these high doses should be decreased as soon as possible. Adults with impairment of hepatic or renal function or both may have reduced ability to metabolize and excrete the drug. In instances of impaired metabolic processes, dosages should be adjusted accordingly. (See discussion under Neonates.) Precise control of concentration of the drug in the blood should be carefully followed in patients with impaired metabolic processes by the available microtechniques.

Pediatric Patients

Dosage of 50 mg/kg/day divided into 4 doses at 6-hour intervals yields blood levels in the range effective against most susceptible organisms. Severe infections (e.g., bacteremia or meningitis), especially when adequate cerebrospinal fluid concentrations are desired, may require dosage up to 100 mg/kg/day; however, it is recommended that dosage be reduced to 50 mg/kg/day as soon as possible. Children with impaired liver or kidney function may retain excessive amounts of the drug.

Neonates

(See section titled ‘‘Gray Syndrome’’under ADVERSE REACTIONS.)

A total of 25 mg/kg/day in 4 equal doses at 6-hour intervals usually produces and maintains concentrations in blood and tissues adequate to control most infections for which the drug is indicated. Increased dosage in these individuals, demanded by severe infections, should be given only to maintain the blood concentration within a therapeutically effective range. After the first two weeks of life, full-term neonates ordinarily may receive up to a total of 50 mg/kg/day equally divided into 4 doses at 6-hour intervals. These dosage recommendations are extremely important because blood concentration in all premature and full-term neonates under two weeks of age differs from that of other infant neonates. This difference is due to variations in the maturity of the metabolic functions of the liver and the kidneys.

When these functions are immature (or seriously impaired in adults), high concentrations of the drug are found which tend to increase with succeeding doses.

Pediatric Patients with Immature Metabolic Processes

In young infants and other pediatric patients in whom immature metabolic functions are suspected, a dose of 25 mg/kg/day will usually produce therapeutic concentrations of the drug in the blood. In this group particularly, the concentration of the drug in the blood should be carefully followed by microtechniques.

HOW SUPPLIED:

Chloramphenicol Sodium Succinate for Injection, USP is freeze-dried in the vial. When reconstituted as directed, each vial contains a sterile solution equivalent to 100 mg of chloramphenicol per mL (1 g/10 mL).

Product No. | NDC No.
1115 | 63323-011-15 | Available in packages of 10 vials.

Preservative Free.

Store at 20° to 25°C (68° to 77°F) [see USP Controlled Room Temperature].

REFERENCES:

1. Clinical and Laboratory Standards Institute (CLSI), Methods for Dilution Antimicrobial Susceptibility Tests for Bacteria that Grow Aerobically; Approved Standard – Tenth Edition. CLSI document M07-A10 [2015], Clinical and Laboratory Standards Institute, 950 West Valley Road, Suite 2500, Wayne, Pennsylvania 19087, USA.
2. Clinical and Laboratory Standards Institute (CLSI). Performance Standards for Antimicrobial Disk Diffusion Susceptibility Tests; Approved Standard – Twelfth Edition. CLSI document M02-A12 [2015]. Clinical and Laboratory Standards Institute, 950 West Valley Road, Suite 2500, Wayne, Pennsylvania 19087, USA.
3. Clinical and Laboratory Standards Institute (CLSI). Performance Standards for Antimicrobial Susceptibility Testing; Twenty-sixth Informational Supplement. CLSI document M100-S26 [2016]. Clinical and Laboratory Standards Institute, 950 West Valley Road, Suite 2500, Wayne, Pennsylvania 19087, USA.

Lake Zurich, IL 60047
www.fresenius-kabi.us

45841H
Revised: October 2016

PACKAGE LABEL

PACKAGE LABEL - PRINCIPAL DISPLAY - Chloramphenicol Sodium Succinate 1 gram Vial Label

Chloramphenicol Sodium Succinate for Injection, USP

1 gram per vial
For intravenous use only.
Preservative free.
Rx only

PACKAGE LABEL - PRINCIPAL DISPLAY - Chloramphenicol Sodium Succinate 1 gram Vial Tray Label

Chloramphenicol Sodium Succinate for Injection, USP

1 gram per vial
For intravenous use only.
Preservative free.
10 x 1 g vials
Rx only